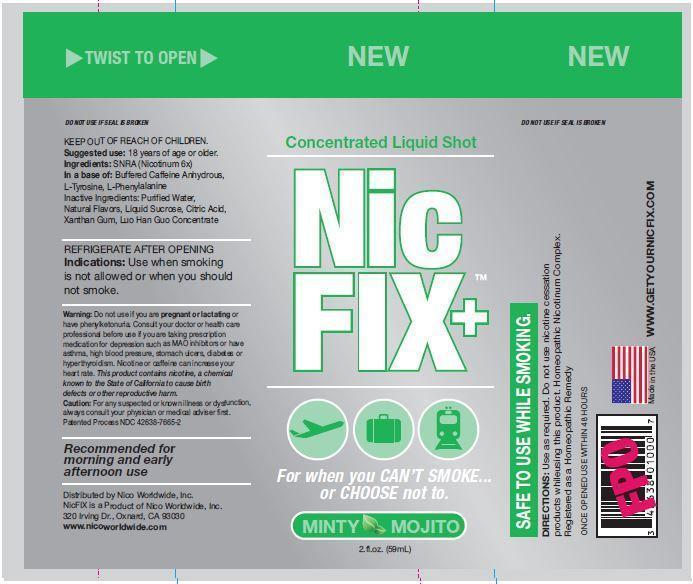 DRUG LABEL: NicFix Plus
NDC: 42638-7664 | Form: LIQUID
Manufacturer: Nico Worldwide, Inc.
Category: homeopathic | Type: HUMAN OTC DRUG LABEL
Date: 20140127

ACTIVE INGREDIENTS: NICOTINE 3 mg/60000 mg; TYROSINE 30 mg/60000 mg; PHENYLALANINE 30 mg/60000 mg; CAFFEINE 75 mg/60000 mg; CITRIC ACID MONOHYDRATE 45 mg/60000 mg
INACTIVE INGREDIENTS: SUCRALOSE 10 mg/60000 mg; SODIUM BENZOATE 10 mg/60000 mg; WATER 59760 mg/60000 mg; XANTHAN GUM 10 mg/60000 mg; SIRAITIA GROSVENORII FRUIT 10 mg/60000 mg

ACTIVE INGREDIENT

Ingredients: SNRA (Nicotinum 6X)

In a base of: buffered caffeine anhydrous, L-tyrosine, L-phenylalanine

PURPOSE

Concentrated Liquid Shot

NicFix+

For when you CAN'T SMOKE... or CHOOSE not to.

Minty Mojito

2 fl. oz. (59 mL)

KEEP OUT OF REACH OF CHILDREN

Suggested Use: 18 years of age or older

INDICATIONS AND USAGE

REFRIGERATE AFTER OPENING

Indications: Use when smoking is not allowed or when you should not smoke.

Recommended for morning and early afternoon use.

WARNINGS

Warning: do not use if you are prenant or lactating or have phenylketonuria. Consult your doctor or health care professional before us if you are taking prescription medication for depression such as MAO inhibitors or have asthma, high blood pressure, stomach ulcers, diabetes, or hyperthyroidism. Nicotine or caffeine can increase your heart rate. This product contains nicotine, a chemical known to the state of California to cause birth defects or other reproductive harms.

Caution: For any suspected or known illness or dysfunction, always consult your physician or medical adviser first.

DOSAGE AND ADMINISTRATION

SAFE TO USE WHILE SMOKING

Directions: Use as required. Do not use nicotine cessation products while using this product. Homeopathic Nicotinum Complex. Registeres as a homeopathic remedy.

www.getyournicfix.com

INACTIVE INGREDIENT

Inactive Ingredients: purified water, natural flavors, liquid sucrose, citric acid, xanthan gum, luo han guo concentrate

OTHER SAFETY INFORMATION

ONCE OPENED USE WITHIN 48 HOURS

Patented process NDC 42638-7685-2

Distributed by Nico Worldwide, Inc.

NicFix is a product of Nico Worldwide, Inc.

320 Irving Dr., Oxnard, CA 93030

www.nicoworldwide.com